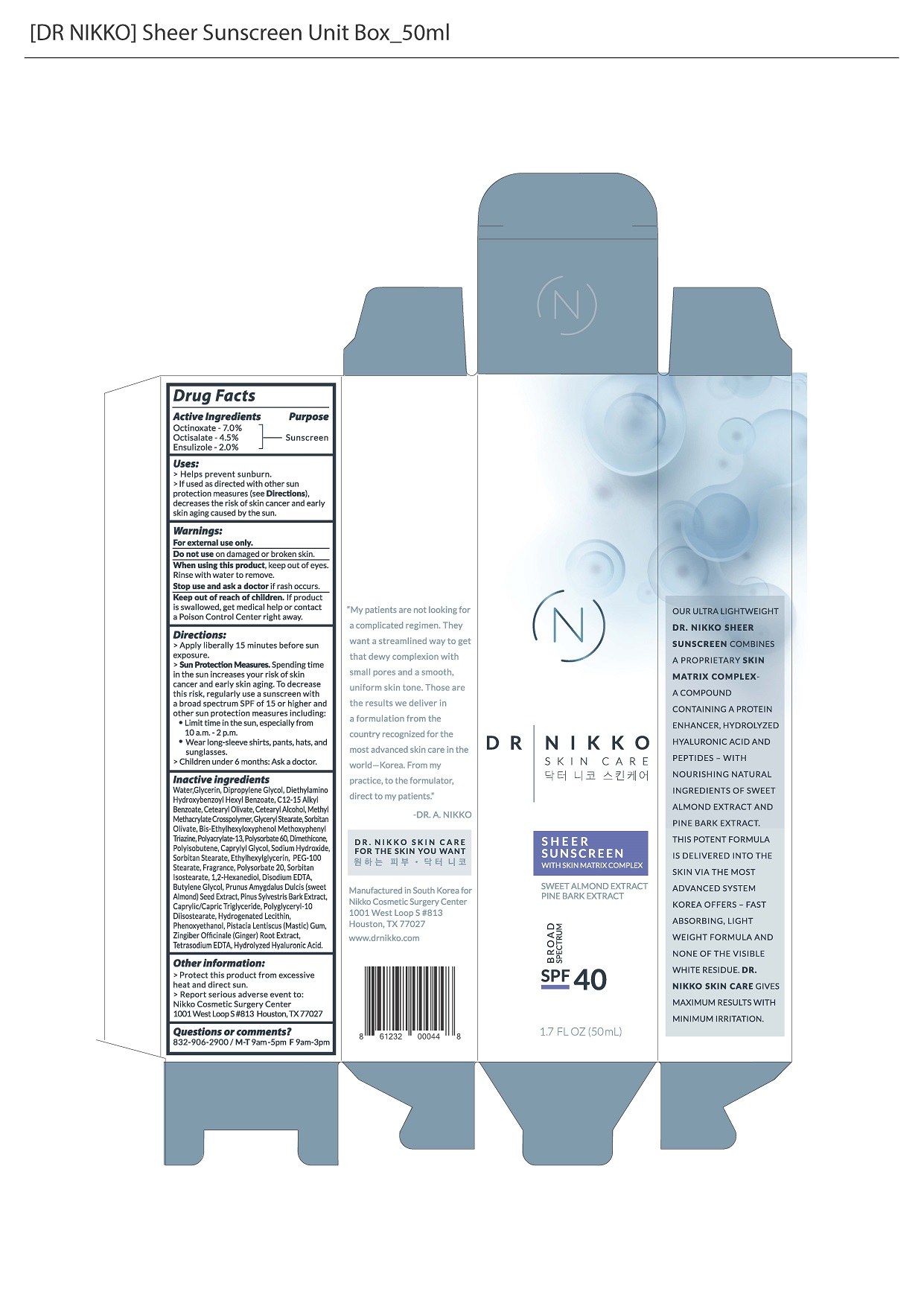 DRUG LABEL: DR NIKKO SHEER SUNSCREEN
NDC: 69133-050 | Form: CREAM
Manufacturer: Cit Co., Ltd.
Category: otc | Type: HUMAN OTC DRUG LABEL
Date: 20180813

ACTIVE INGREDIENTS: OCTINOXATE 7 g/100 mL; ENSULIZOLE 2 g/100 mL; OCTISALATE 4.5 g/100 mL
INACTIVE INGREDIENTS: WATER; GLYCERIN

ACTIVE INGREDIENT

octinoxate, octisalate, ensulizole

INACTIVE INGREDIENT

water, glycerin, dipropylene glycol, etc.

PURPOSE

helps prevent sunburn

WARNINGS

1. If the following symptoms occur after product use, stop using the product immediately and consult a dermatologist (continuous use can exacerbate the symptoms).
1) Occurrence of red spots, swelling, itchiness, and other irritation
2) If the symptoms above occur after the application area is exposed to direct sunlight

2. Do not use on open wounds, eczema, and other irritations
3. Precaution for Storage and Handling
1) Close the lid after use
2) Keep out of reach of infants and children
3) Do not to store in a place with high/low temperature and exposed to direct sunlight

4. Use as avoiding eye areas.

Keep out of reach of children.

INDICATIONS AND USAGE

Apply liberally 15 minutes before sun exposure

DOSAGE AND ADMINISTRATION

external use only